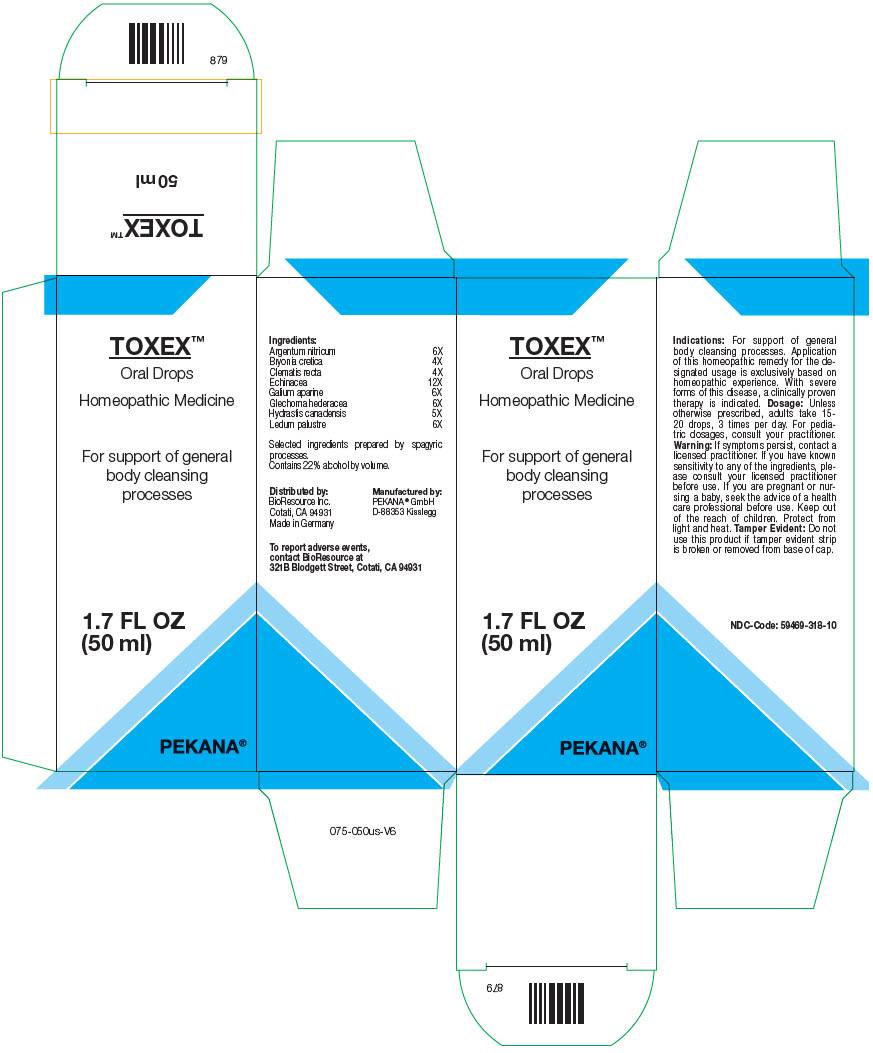 DRUG LABEL: TOXEX
NDC: 59469-318 | Form: SOLUTION/ DROPS
Manufacturer: PEKANA Naturheilmittel GmbH
Category: homeopathic | Type: HUMAN OTC DRUG LABEL
Date: 20230111

ACTIVE INGREDIENTS: SILVER NITRATE 6 [hp_X]/50 mL; BRYONIA CRETICA SUBSP. DIOICA ROOT 4 [hp_X]/50 mL; CLEMATIS RECTA FLOWERING TOP 4 [hp_X]/50 mL; GOLDENSEAL 5 [hp_X]/50 mL; ECHINACEA, UNSPECIFIED 12 [hp_X]/50 mL; GALIUM APARINE WHOLE 6 [hp_X]/50 mL; GLECHOMA HEDERACEA FLOWERING TOP 6 [hp_X]/50 mL; RHODODENDRON TOMENTOSUM LEAFY TWIG 6 [hp_X]/50 mL
INACTIVE INGREDIENTS: WATER; ALCOHOL

TOXEX™

ACTIVE INGREDIENT

Ingredients:
Argentum nitricum | 6X
Bryonia cretica | 4X
Clematis recta | 4X
Echinacea | 12X
Galium aparine | 6X
Glechoma hederacea | 6X
Hydrastis canadensis | 5X
Ledum palustre | 6X

INACTIVE INGREDIENT

Selected ingredients prepared by spagyric processes.

Contains 22% alcohol by volume.

Indications

PURPOSE

For support of general body cleansing processes. Application of this homeopathic remedy for the designated usage is exclusively based on homeopathic experience. With severe forms of this disease, a clinically proven therapy is indicated.

Dosage

Unless otherwise prescribed, adults take 15-20 drops, 3 times per day. For pediatric dosages, consult your practitioner.

Warning

If symptoms persist, contact a licensed practitioner. If you have known sensitivity to any of the ingredients, please consult your licensed practitioner before use. If you are pregnant or nursing a baby, seek the advice of a health care professional before use.

Keep out of the reach of children.

STORAGE AND HANDLING

Protect from light and heat.

Tamper Evident

Do not use this product if tamper evident strip is broken or removed from base of cap.

QUESTIONS

To report adverse events, contact BioResource at 321B Blodgett Street, Cotati, CA 94931

Distributed by:
BioResource Inc.
Cotati, CA 94931

Manufactured by:
PEKANA® GmbH
D-88353 Kisslegg

PRINCIPAL DISPLAY PANEL - 50 ml Bottle Box

TOXEX™

Oral Drops

Homeopathic Medicine

For support of general
body cleansing
processes

1.7 FL OZ
(50 ml)

PEKANA®